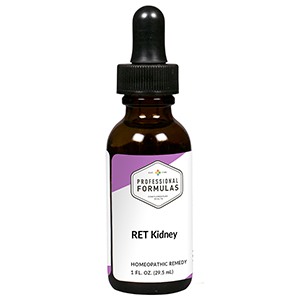 DRUG LABEL: RET Kidney
NDC: 63083-7005 | Form: LIQUID
Manufacturer: Professional Complementary Health Formulas
Category: homeopathic | Type: HUMAN OTC DRUG LABEL
Date: 20190815

ACTIVE INGREDIENTS: POPULUS TREMULA FLOWERING TOP 3 [hp_X]/29.5 mL; MIMULUS GUTTATUS FLOWERING TOP 3 [hp_X]/29.5 mL; PINUS SYLVESTRIS FLOWERING TOP 3 [hp_X]/29.5 mL; CALCIUM SULFATE ANHYDROUS 3 [hp_X]/29.5 mL; POTASSIUM PHOSPHATE, UNSPECIFIED FORM 3 [hp_X]/29.5 mL; SILVER NITRATE 30 [hp_X]/29.5 mL; GOLD 30 [hp_X]/29.5 mL; OYSTER SHELL CALCIUM CARBONATE, CRUDE 30 [hp_X]/29.5 mL; GRAPHITE 30 [hp_X]/29.5 mL; STRYCHNOS IGNATII SEED 30 [hp_X]/29.5 mL; LYCOPODIUM CLAVATUM SPORE 30 [hp_X]/29.5 mL; PHOSPHORUS 30 [hp_X]/29.5 mL; SEPIA OFFICINALIS JUICE 30 [hp_X]/29.5 mL
INACTIVE INGREDIENTS: ALCOHOL; WATER

RET5

ACTIVE INGREDIENTS

Aspen flower essence 3X
Mimulus flower essence 3X
Pine flower essence 3X
Calcarea sulphurica 3X, 6X, 30X
Kali phosphoricum 3X, 6X, 30X
and all the following at 30X, 100X, 200X:
Argentum nitricum
Aurum metallicum
Calcarea carbonica
Graphites
Ignatia amara
Lycopodium clavatum
Phosphorus
Sepia

QUESTIONS

Professional Formulas

PO Box 2034 Lake Oswego, OR 97035

INDICATIONS

Temporarily relieves fear, worry, dread, lack of courage, shame, self-reproach, anxiousness, unworthiness, or irritability.*

PURPOSE

*Claims based on traditional homeopathic practice, not accepted medical evidence. Not FDA evaluated.

WARNINGS

In case of overdose, get medical help or contact a poison control center right away.

Keep out of the reach of children.

PREGNANCY OR BREAST FEEDING

If pregnant or breastfeeding, ask a healthcare professional before use.

DIRECTIONS

Place drops under tongue 30 minutes before/after meals. Adults and children 12 years and over: Take 5 drops up to 4 times per day for up to one month. Consult a physician for use in children under 12 years of age.

OTHER INFORMATION

Tamper resistant. If seal is broken, do not use. After opening, close container tightly and store at room temperature away from heat.

INACTIVE INGREDIENTS

20% ethanol, purified water.

LABEL

Est 1985

Professional Formulas

Complementary Health

RET Kidney

Homeopathic Remedy

1 FL. OZ. (29.5 mL)